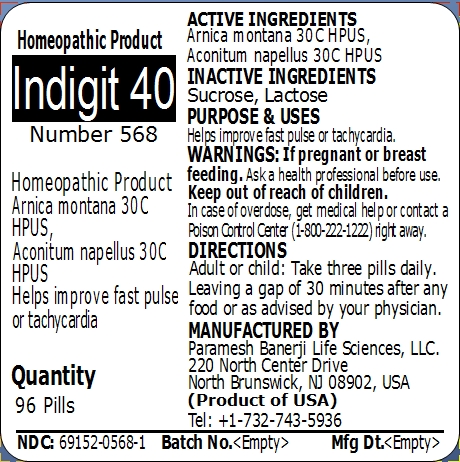 DRUG LABEL: Indigit 40 (Number 568)
NDC: 69152-0568 | Form: PELLET
Manufacturer: Paramesh Banerji Life Sciences LLC
Category: homeopathic | Type: HUMAN OTC DRUG LABEL
Date: 20150225

ACTIVE INGREDIENTS: ARNICA MONTANA 30 [hp_C]/1 1; ACONITUM NAPELLUS 30 [hp_C]/1 1
INACTIVE INGREDIENTS: SUCROSE; LACTOSE

Active Ingredients

Arnica montana 30C HPUS, Aconitum napellus 30C HPUS

Inactive Ingredients

Sucrose, Lactose

Purpose

Helps improve fast pulse or tachycardia

Uses

Helps improve fast pulse or tachycardia

Warnings

If pregnant or breast feeding ask a health professional before use.

Keep out of reach of children. In case of overdose, get medical help or contact a Poison Control Center (1-800-222-1222) right away.

Direction

Adult or child: Take three pills daily. Leaving a gap of 30 minutes after any food or as advised by your physician.

Manufactured by

Paramesh Banerji Life Sciences, LLC

220 North Center Drive

North Brunswick, NJ 08902, USA

Product of USA

Tel: +1-732-743-5936

Principal Display Panel

Homeopathic Product

Indigit 40

Number 568

Homeopathic Product

Arnica montana 30C HPUS, Aconitum napellus 30C HPUS

Helps improve fast pulse or tachycardia

Quantity

96 Pills